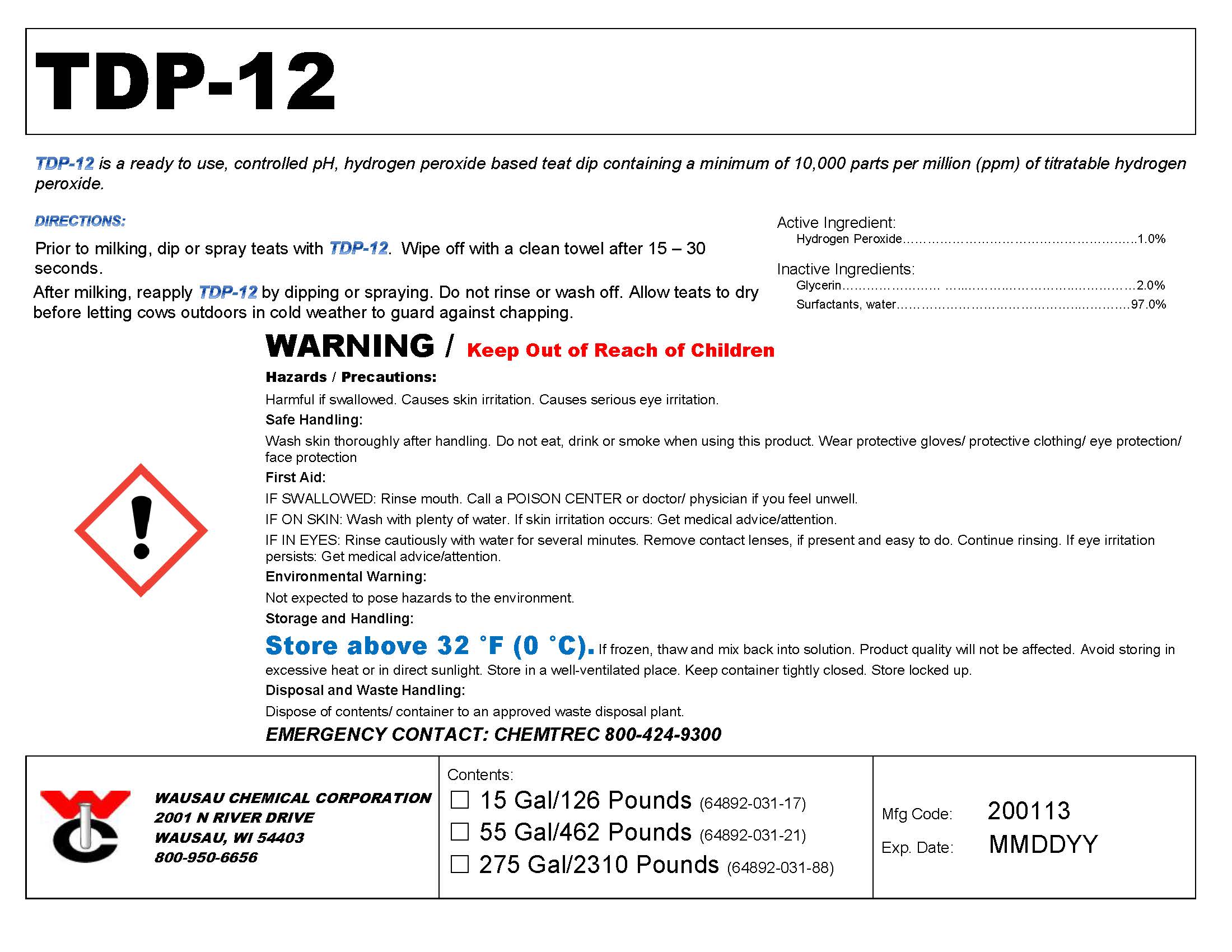 DRUG LABEL: TDP-12
NDC: 64892-031 | Form: SOLUTION
Manufacturer: Wausau Chemical
Category: animal | Type: OTC ANIMAL DRUG LABEL
Date: 20200114

ACTIVE INGREDIENTS: HYDROGEN PEROXIDE 10000 mg/1 L

TDP-12
Hydrogen Peroxide Teat Dip

DISPOSAL AND WASTE HANDLING

Dispose of contents/container to an approved waste disposal plant.

ENVIRONMENTAL WARNING

Not expected to pose hazards to the environment.

GENERAL PRECAUTIONS

WARNING / Keep Out of Reach of Children

Harmful if swallowed. Causes skin irritation. Causes serious eye irritation.

First Aid:

IF SWALLOWED: Rinse mouth. Call a POISON CENTER or doctor/ physician if you feel unwell.

IF ON SKIN: Wash with plenty of water. If skin irritation occurs: Get medical advice/attention.

IF IN EYES: Rinse cautiously with water for several minutes. Remove contact lenses, if present and easy to do. Continue rinsing. If eye irritation persists: Get medical advice/attention.

SAFE HANDLING WARNING

Wash skin thoroughly after handling. Do not eat, drink or smoke when using this product. Wear protective gloves/ protective clothing/ eye protection/ face protection.

STORAGE AND HANDLING

Store above 32 °F (0 °C). If frozen, thaw and mix back into solution. Product quality will not be affected.

Avoid storing in excessive heat or in direct sunlight. Store in a well-ventilated place. Keep container tightly closed. Store locked up.

DIRECTIONS:

Prior to milking, dip or spray teats with TDP-12. Wipe off with a clean towel after 15 – 30 seconds.

After milking, reapply TDP-12 by dipping or spraying. Do not rinse or wash off. Allow teats to dry before letting cows outdoors in cold weather to guard against chapping.

Active Ingredient:
Hydrogen Peroxide………………………………………………………………1.0%

Wausau Chemical Corporation

2001 N River Drive

Wausau, WI 54403

800-950-6656